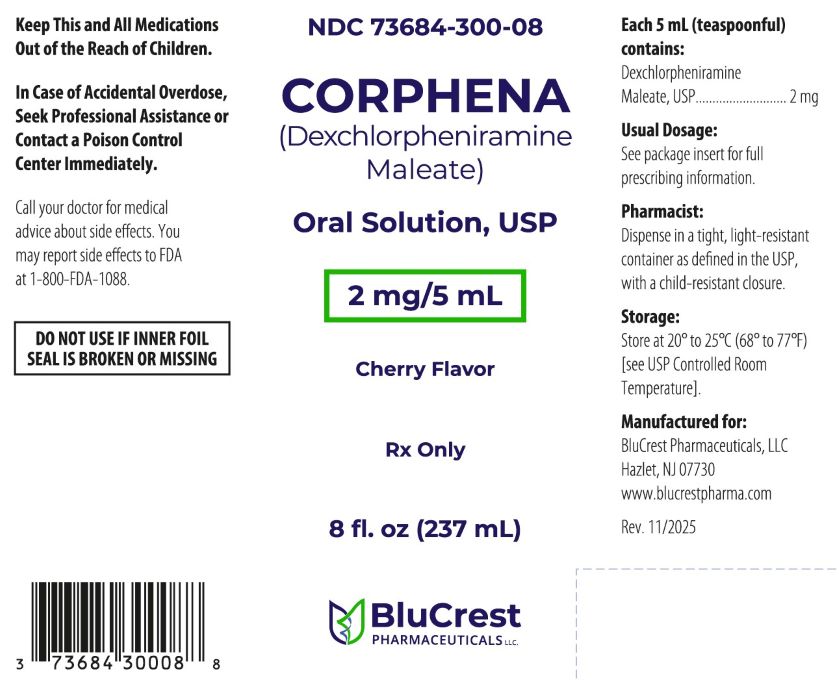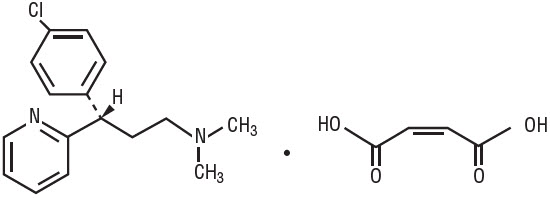 DRUG LABEL: Corphena
NDC: 73684-300 | Form: SOLUTION
Manufacturer: BluCrest Pharmaceuticals LLC
Category: prescription | Type: HUMAN PRESCRIPTION DRUG LABEL
Date: 20251222

ACTIVE INGREDIENTS: DEXCHLORPHENIRAMINE MALEATE 2 mg/5 mL
INACTIVE INGREDIENTS: CITRIC ACID MONOHYDRATE; FD&C RED NO. 40; GLYCERIN; MENTHOL, UNSPECIFIED FORM; METHYLPARABEN; PROPYLENE GLYCOL; PROPYLPARABEN; WATER; TRISODIUM CITRATE DIHYDRATE; SUCROSE; CHERRY

CORPHONA
(dexchlorpheniramine maleate) Oral Solution, USP

Rx only

DESCRIPTION

Each 5 mL (teaspoonful) contains:
Dexchlorpheniramine Maleate, USP | 2 mg

Dexchlorpheniramine Maleate, USP, an antihistamine agent, is a white, odorless crystalline powder that is freely soluble in water. The molecular formula is C16H19ClN2∙ C4H4O4, designated chemically as (+)-2-[p-Chloro-α-[2-(dimethylamino)ethyl]benzyl] pyridine maleate (1:1).

M.W. = 390.86

Inactive Ingredients:Citric acid, cherry flavoring, FD&C Red No. 40, glycerin, menthol, methylparaben, propylene glycol, propylparaben, purified water, sodium citrate dihydrate, and sugar.

CLINICAL PHARMACOLOGY

Dexchlorpheniramine maleate is an antihistamine with anticholinergic (drying) and sedative side effects. Antihistamines appear to compete with histamine for cell receptor sites on effector cells.

INDICATIONS AND USAGE

Perennial and seasonal allergic rhinitis

Vasomotor rhinitis

Allergic conjunctivitis due to inhalant allergens and foods

Mild, uncomplicated allergic skin manifestations of urticaria and angioedema

Amelioration of allergic reactions to blood or plasma

Dermographism

As therapy for anaphylactic reactions adjunctive to epinephrine and other standard measures after the acute manifestations have been controlled.

CONTRAINDICATIONS

-

Use in Newborn or Premature Infants

This drug should not be used in newborn or premature infants.

Use in Nursing Mothers

Because of the higher risk of antihistamines for infants generally and for newborns and prematures in particular, antihistamine therapy is contraindicated in nursing mothers.

Use in Lower Respiratory Disease

Antihistamines should NOTbe used to treat lower respiratory tract symptoms including asthma.

Antihistamines are also contraindicated in the following conditions:

1. Hypersensitivity to dexchlorpheniramine maleate or other antihistamines of similar chemical structure
2. Monoamine oxidase inhibitor therapy (See Drug Interactionsection)

WARNINGS

Antihistamines should be used with considerable caution in patients with:

1. Narrow angle glaucoma
2. Stenosing peptic ulcer
3. Pyloroduodenal obstruction
4. Symptomatic prostatic hypertrophy
5. Bladder neck obstruction

Use in Children

In infants and children, especially, antihistamines in overdosagemay cause hallucinations, convulsions, or death.

As in adults, antihistamines may diminish mental alertness in children. In the young child, particularly, they may produce excitation.

Use in Pregnancy

Experience with this drug in pregnant women is inadequate to determine whether there exists a potential for harm to the developing fetus.

Use with CNS Depressants

CORPHENA Oral Solution has additive effects with alcohol and other CNS depressants (hypnotics, sedatives, tranquilizers, etc.).

Use in Activities Requiring Mental Alertness

Patients should be warned about engaging in activities requiring mental alertness such as driving a car or operating appliances, machinery, etc.

Use in the Elderly (approximately 60 years or older)

Antihistamines are more likely to cause dizziness, sedation, and hypotension in elderly patients.

PRECAUTIONS

CORPHENA Oral Solution has an atropine-like action and, therefore, should be used with caution in patients with:

History of bronchial asthma
Increased intraocular pressure Hyperthyroidism
Cardiovascular disease
Hypertension

Drug Interaction

MAO inhibitors prolong and intensify the anticholinergic (drying) effects of antihistamines.

ADVERSE REACTIONS

1. General:Urticaria, drug rash, anaphylactic shock, photosensitivity, excessive perspiration, chills, dryness of mouth, nose and the throat.
2. Cardiovascular System:Hemolytic anemia, thrombocytopenia, agranulocytosis.
3. Hematologic System:Hemolytic anemia, thrombocytopenia, agranulocytosis.
4. Nervous System:Sedation, sleepiness, dizziness, disturbed coordination, fatigue, confusion, restlessness, excitation, nervousness, tremor, irritability, insomnia, euphoria, paresthesias, blurred vision, diplopia, vertigo, tinnitus, acute labyrinthitis, hysteria, neuritis, convulsions.
5. G.I. System:Epigastric distress, anorexia, nausea, vomiting, diarrhea, constipation.
6. G.U. System:Urinary frequency, difficult urination, urinary retention, early menses.
7. Respiratory System:Thickening of bronchial secretions, tightness of chest and wheezing, nasal stuffiness.

Call your doctor for medical advice about side effects. You may voluntarily report side effects to FDA at 1-800-FDA-1088.Questions or comments? Call BluCrest Pharmaceuticals, LLC at 1-844-700-5011.

OVERDOSAGE

Antihistamine overdosage reactions may vary from central nervous system depression to stimulation. Stimulation is particularly likely in children. Atropine-like signs and symptoms—dry mouth, fixed, dilated pupils, flushing, and gastrointestinal symptoms may also occur.

If vomiting has not occurred spontaneouslythe patient should be induced to vomit. This is best done by having the patient drink a glass of water or milk after which the patient should be made to gag. Precautions against aspiration must be taken, especially in infants and children.

Saline cathartics, such as milk of magnesia, draw water into the bowel by osmosis and therefore, are valuable for their action in rapid dilution of bowel content.

Stimulants should not be used.

Vasopressors may be used to treat hypotension.

DOSAGE AND ADMINISTRATION

DOSAGE SHOULD BE INDIVIDUALIZED ACCORDING TO THE NEEDS AND THE RESPONSE OF THE PATIENT.

Recommended Dosage

Adults and Children 12 years of age and older: 2 mg (1 teaspoonful)

Children 6 to 11 years: 1 mg (1/2 teaspoonful)

Children 2 to 5 years: 0.5 mg (1/4 teaspoonful)

Doses are generally given every 4 to 6 hours.

HOW SUPPLIED

CORPHENA Oral Solution is supplied as a red colored, cherry flavored liquid in the following sizes:

8 fl oz (237 mL), NDC 73684-300-08

RECOMMENDED STORAGE

Store at 20° to 25°C (68° to 77°F) [see USP Controlled Room Temperature].

Dispense in a tight, light-resistant container as defined in the USP, with child-resistant closure.

Rx Only

Manufactured for:

BluCrest Pharmaceuticals, LLC

Hazlet, NJ 07730

www.blucrestpharma.com

Rev. 11/2025